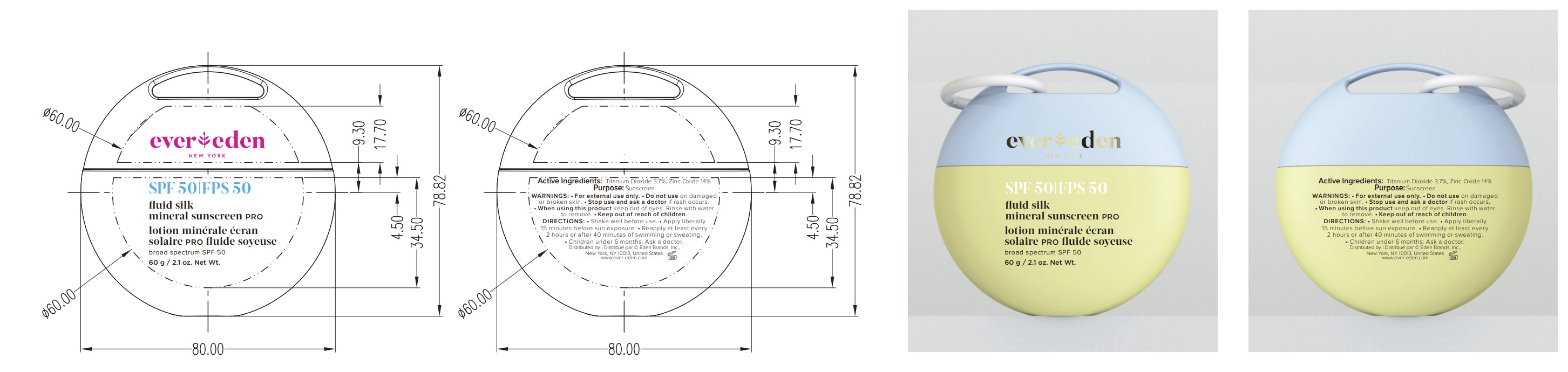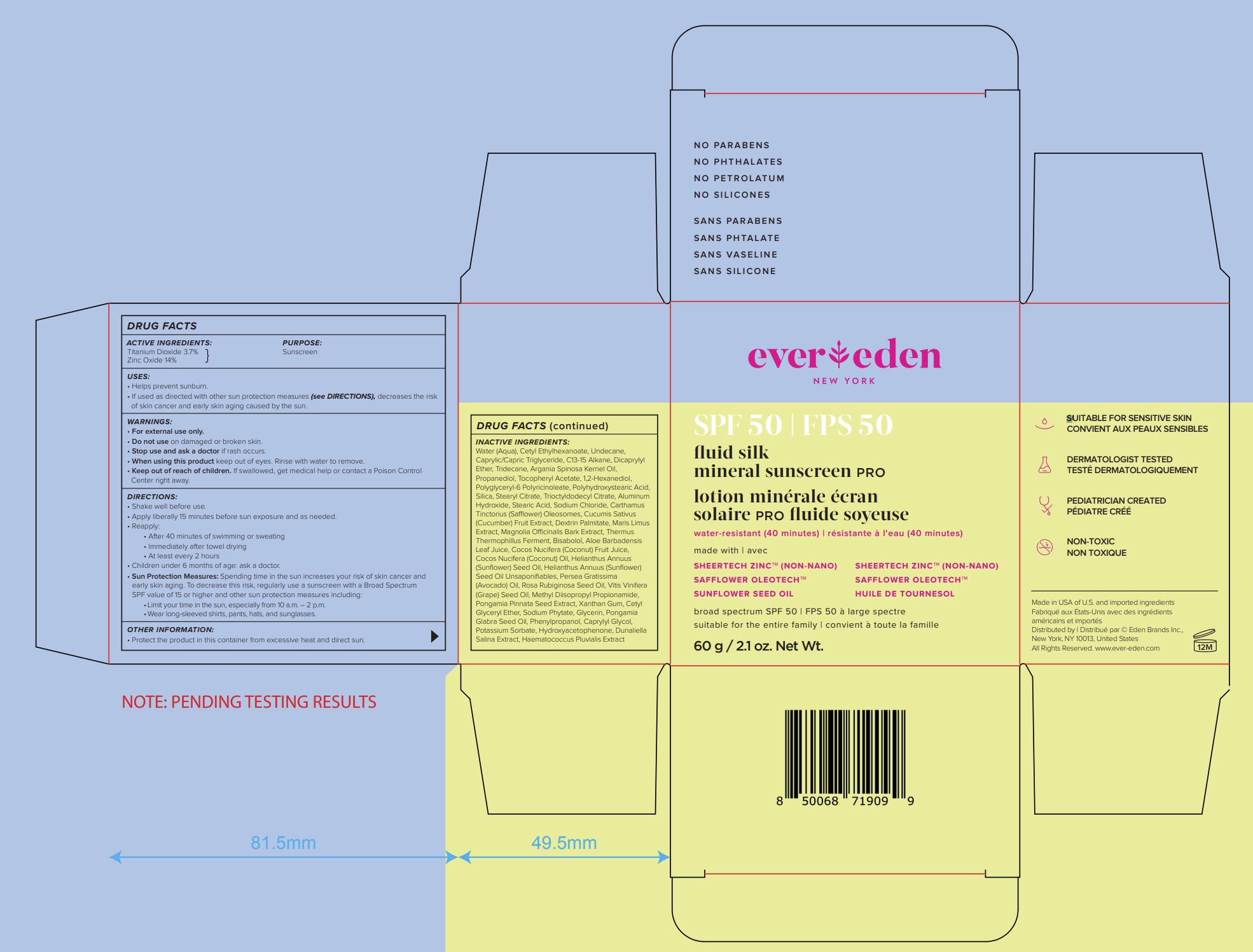 DRUG LABEL: Evereden Fluid Silk Mineral Sunscreen PRO SPF50
NDC: 72113-110 | Form: LOTION
Manufacturer: Eden Brands Inc.
Category: otc | Type: HUMAN OTC DRUG LABEL
Date: 20250127

ACTIVE INGREDIENTS: ZINC OXIDE 140 mg/1 g; TITANIUM DIOXIDE 37 mg/1 g
INACTIVE INGREDIENTS: PROPANEDIOL; 1,2-HEXANEDIOL; SILICON DIOXIDE; CARTHAMUS TINCTORIUS (SAFFLOWER) OLEOSOMES; ROSA RUBIGINOSA SEED OIL; POLYHYDROXYSTEARIC ACID (2300 MW); PHENYLPROPANOL; WATER; UNDECANE; DICAPRYLYL ETHER; ARGANIA SPINOSA KERNEL OIL; CETYL ETHYLHEXANOATE; STEARIC ACID; POTASSIUM SORBATE; BISABOLOL; HELIANTHUS ANNUUS (SUNFLOWER) SEED OIL; SODIUM CHLORIDE; DEXTRIN PALMITATE (CORN; 20000 MW); HYDROXYACETOPHENONE; DUNALIELLA SALINA; C13-15 ALKANE; TRIDECANE; STEARYL CITRATE; TRIOCTYLDODECYL CITRATE; ALUMINUM HYDROXIDE; THERMUS THERMOPHILUS LYSATE; COCOS NUCIFERA (COCONUT) OIL; CUCUMBER; ALOE BARBADENSIS LEAF JUICE; VITIS VINIFERA (GRAPE) SEED OIL; PONGAMIA GLABRA SEED OIL; MAGNOLIA OFFICINALIS BARK; COCOS NUCIFERA (COCONUT) FRUIT JUICE; HELIANTHUS ANNUUS (SUNFLOWER) SEED OIL UNSAPONIFIABLES; PERSEA GRATISSIMA (AVOCADO) OIL; METHYL DIISOPROPYL PROPIONAMIDE; PONGAMIA PINNATA SEED; XANTHAN GUM; GLYCERIN; CETYL GLYCERYL ETHER; SODIUM PHYTATE; CAPRYLYL GLYCOL; CAPRYLIC/CAPRIC TRIGLYCERIDE; .ALPHA.-TOCOPHEROL ACETATE; POLYGLYCERYL-6 POLYRICINOLEATE; HAEMATOCOCCUS PLUVIALIS

ACTIVE INGREDIENTS:

Titanium Dioxide 3.7% Zinc Oxide 14%

PURPOSE:

Sunscreen

USES:

• Helps prevent sunburn. • If used as directed with other sun protection measures (see DIRECTIONS), decreases the risk of skin cancer and early skin aging caused by the sun.

WARNINGS:

• For external use only.

• Do not use on damaged or broken skin.

• Stop use and ask a doctor if rash occurs.

• When using this product keep out of eyes. Rinse with water to remove.

Keep out of reach of children. If swallowed, get medical help or contact a Poison Control Center right away.

DIRECTIONS:

• Shake well before use.

• Apply liberally 15 minutes before sun exposure and as needed.

• Reapply: • After 40 minutes of swimming or sweating • Immediately after towel drying • At least every 2 hours

• Children under 6 months of age: ask a doctor. •

Sun Protection Measures: Spending time in the sun increases your risk of skin cancer and early skin aging. To decrease this risk, regularly use a sunscreen with a Broad Spectrum SPF value of 15 or higher and other sun protection measures including:

• Limit your time in the sun, especially from 10 a.m. – 2 p.m.

• Wear long-sleeved shirts, pants, hats, and sunglasses.

OTHER INFORMATION:

• Protect the product in this container from excessive heat and direct sun.

INACTIVE INGREDIENTS:

Water (Aqua), Cetyl Ethylhexanoate, Undecane, Caprylic/Capric Triglyceride, C13-15 Alkane, Dicaprylyl Ether, Tridecane, Argania Spinosa Kernel Oil, Propanediol, Tocopheryl Acetate, 1,2-Hexanediol, Polyglyceryl-6 Polyricinoleate, Polyhydroxystearic Acid, Silica, Stearyl Citrate, Trioctyldodecyl Citrate, Aluminum Hydroxide, Stearic Acid, Sodium Chloride, Carthamus Tinctorius (Safflower) Oleosomes, Cucumis Sativus (Cucumber) Fruit Extract, Dextrin Palmitate, Maris Limus Extract, Magnolia Officinalis Bark Extract, Thermus Thermophillus Ferment, Bisabolol, Aloe Barbadensis Leaf Juice, Cocos Nucifera (Coconut) Fruit Juice, Cocos Nucifera (Coconut) Oil, Helianthus Annuus (Sunflower) Seed Oil, Helianthus Annuus (Sunflower) Seed Oil Unsaponifiables, Persea Gratissima (Avocado) Oil, Rosa Rubiginosa Seed Oil, Vitis Vinifera (Grape) Seed Oil, Methyl Diisopropyl Propionamide, Pongamia Pinnata Seed Extract, Xanthan Gum, Cetyl Glyceryl Ether, Sodium Phytate, Glycerin, Pongamia Glabra Seed Oil, Phenylpropanol, Caprylyl Glycol, Potassium Sorbate, Hydroxyacetophenone, Dunaliella Salina Extract, Haematococcus Pluvialis Extract